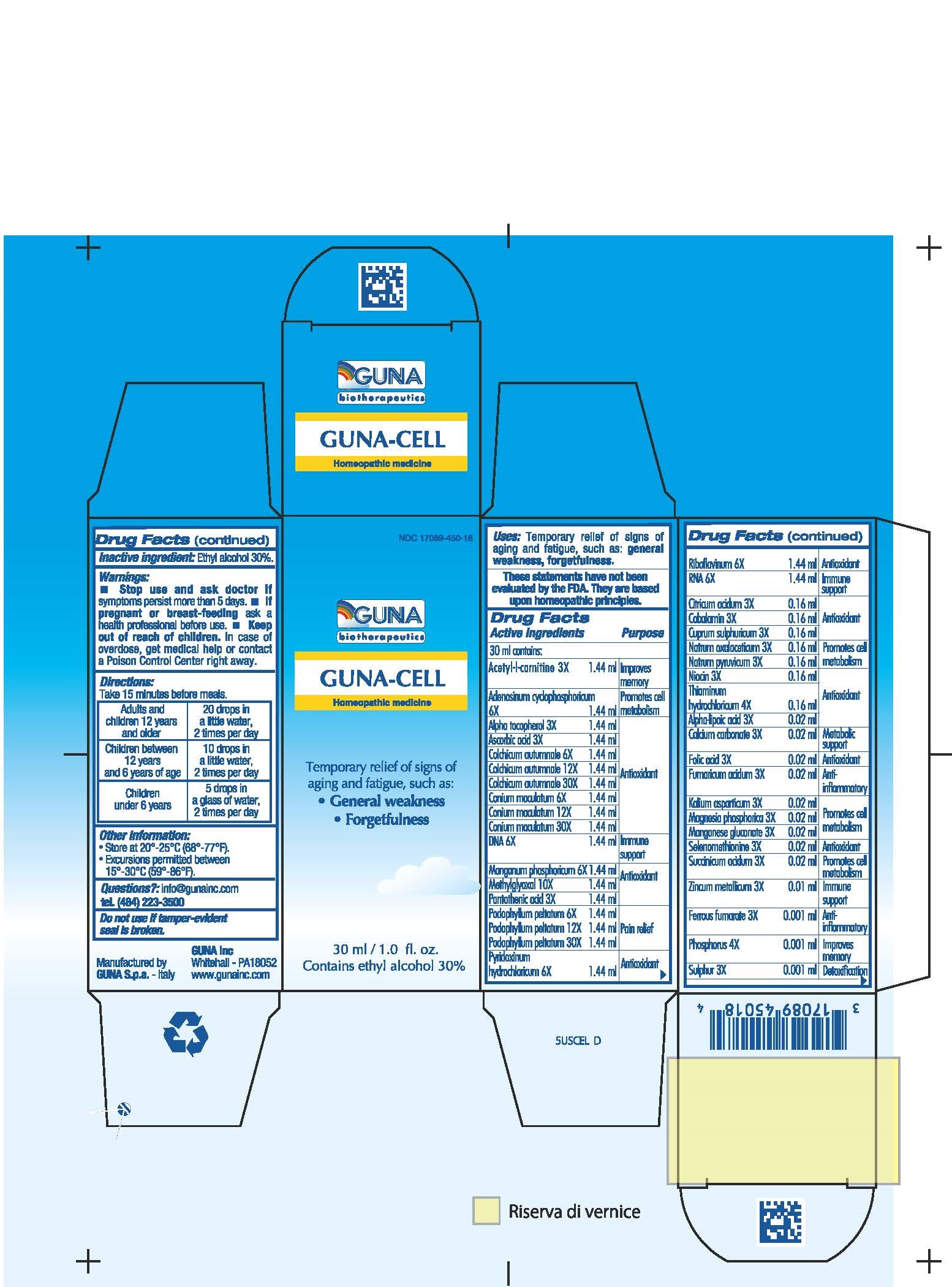 DRUG LABEL: GUNA-CELL
NDC: 17089-450 | Form: SOLUTION/ DROPS
Manufacturer: Guna spa
Category: homeopathic | Type: HUMAN OTC DRUG LABEL
Date: 20181221

ACTIVE INGREDIENTS: ACETYLCARNITINE 3 [hp_X]/30 mL; ADENOSINE CYCLIC PHOSPHATE 6 [hp_X]/30 mL; .ALPHA.-LIPOIC ACID 3 [hp_X]/30 mL; .ALPHA.-TOCOPHEROL ACETATE, DL- 3 [hp_X]/30 mL; ASCORBIC ACID 3 [hp_X]/30 mL; CALCIUM CARBONATE 3 [hp_X]/30 mL; CITRIC ACID MONOHYDRATE 3 [hp_X]/30 mL; COBALAMIN 3 [hp_X]/30 mL; COLCHICUM AUTUMNALE BULB 6 [hp_X]/30 mL; CONIUM MACULATUM FLOWERING TOP 6 [hp_X]/30 mL; CUPRIC SULFATE 3 [hp_X]/30 mL; HERRING SPERM DNA 6 [hp_X]/30 mL; FERROUS FUMARATE 3 [hp_X]/30 mL; FOLIC ACID 3 [hp_X]/30 mL; FUMARIC ACID 3 [hp_X]/30 mL; PYRUVALDEHYDE 10 [hp_X]/30 mL; POTASSIUM ASPARTATE 3 [hp_X]/30 mL; MAGNESIUM PHOSPHATE, TRIBASIC, PENTAHYDRATE 3 [hp_X]/30 mL; MANGANESE GLUCONATE 3 [hp_X]/30 mL; MANGANESE PHOSPHATE, DIBASIC 6 [hp_X]/30 mL; SODIUM DIETHYL OXALACETATE 3 [hp_X]/30 mL; SODIUM PYRUVATE 3 [hp_X]/30 mL; NIACIN 3 [hp_X]/30 mL; PANTOTHENIC ACID 3 [hp_X]/30 mL; PHOSPHORUS 4 [hp_X]/30 mL; PODOPHYLLUM PELTATUM ROOT 6 [hp_X]/30 mL; PYRIDOXINE HYDROCHLORIDE 6 [hp_X]/30 mL; RIBOFLAVIN 6 [hp_X]/30 mL; SACCHAROMYCES CEREVISIAE RNA 6 [hp_X]/30 mL; SELENOMETHIONINE 3 [hp_X]/30 mL; SUCCINIC ACID 3 [hp_X]/30 mL; SULFUR 3 [hp_X]/30 mL; THIAMINE HYDROCHLORIDE 4 [hp_X]/30 mL; ZINC 3 [hp_X]/30 mL
INACTIVE INGREDIENTS: ALCOHOL

GUNA-CELL

ACTIVE INGREDIENTS/PURPOSE

ACETYL-L-CARNITINE 3X IMPROVES MEMORY
ADENOSINUM CYCLOPHOSPHORICUM 6X PROMOTES CELL METABOLISM
A-LIPOICUM ACIDUM 3X ANTIOXIDANT
ALPHA TOCOPHEROL 3X ANTIOXIDANT
ASCORBIC ACID 3X ANTIOXIDANT
CALCIUM CARBONATE 3X METABOLIC SUPPORT
CITRICUM ACIDUM 3X ANTIOXIDANT
COBALAMIN 3X ANTIOXIDANT
COLCHICUM AUTUMNALE 6X 12X 30X ANTIOXIDANT
CONIUM MACULATUM 6X 12X 30X ANTIOXIDANT
CUPRUM SULPHURICUM 3X ANTIOXIDANT
DNA 6X IMMUNE SUPPORT
FERRUM FUMARICUM 3X ANTI-INFLAMMATORY
FOLIC ACID 3X ANTIOXIDANT
FUMARICUM ACIDUM 3X ANTI-INFLAMMATORY
KALIUM ASPARTICUM 3X PROMOTES CELL METABOLISM
MAGNESIA PHOSPHORICA 3X PROMOTES CELL METABOLISM
MANGANESE GLUCONATE 3X PROMOTES CELL METABOLISM
MANGANUM PHOSPHORICUM 6X ANTIOXIDANT
METHYLGLYOXAL 10X ANTIOXIDANT
NATRUM OXALACETICUM 3X PROMOTES CELL METABOLISM
NATRUM PYRUVICUM 3X PROMOTES CELL METABOLISM
NIACIN 3X ANTIOXIDANT
PANTOTHENIC ACID 3X ANTIOXIDANT
PHOSPHORUS 4X IMPROVES MEMORY
PODOPHYLLUM PELTATUM 6X 12X 30X PAIN RELIEF
PYRIDOXINUM HYDROCHLORICUM 6X ANTIOXIDANT
RIBOFLAVINUM 6X ANTIOXIDANT
RNA 6X IMMUNE SUPPORT
SELENOMETHIONINE 3X ANTIOXIDANT
SUCCINICUM ACIDUM 3X PROMOTE CELL METABOLISM
SULPHUR 3X DETOXIFICATION
THIAMINUM HYDROCHLORICUM 4X ANTIOXIDANT
ZINCUM METALLICUM 3X IMMUNE SUPPORT

USES

For the temporary relief of signs of aging and fatigue such as:

- General weakness
- Forgetfulness.

WARNINGS

- Stop use and ask doctor if symptoms persist more than 5 days.
- If pregnant or breast-feeding ask a health professional before use.
- Keep out of reach of children. In case of overdose, get medical help or contact a Poison Control Center right away.
- Contains ethyl alcohol 30%

PREGNANCY

If pregnant of breast-feeding ask a doctor before use

WARNINGS

Keep out of the reach of children

DIRECTIONS

Take 15 minutes before meals
Adults and children 12 years and older 20 drops in a little water 2 times per day
Children between 12 years and 6 years of age. 10 drops in a little water 2 times per day
Children under 6 years 5 drops in a glass of water 2 times per day

QUESTIONS

Questions?: info@gunainc.com, tel. (484) 223-3500

Inactive ingredient: Ethyl alcohol.

INDICATIONS AND USAGE

Take 15 minutes before meals.